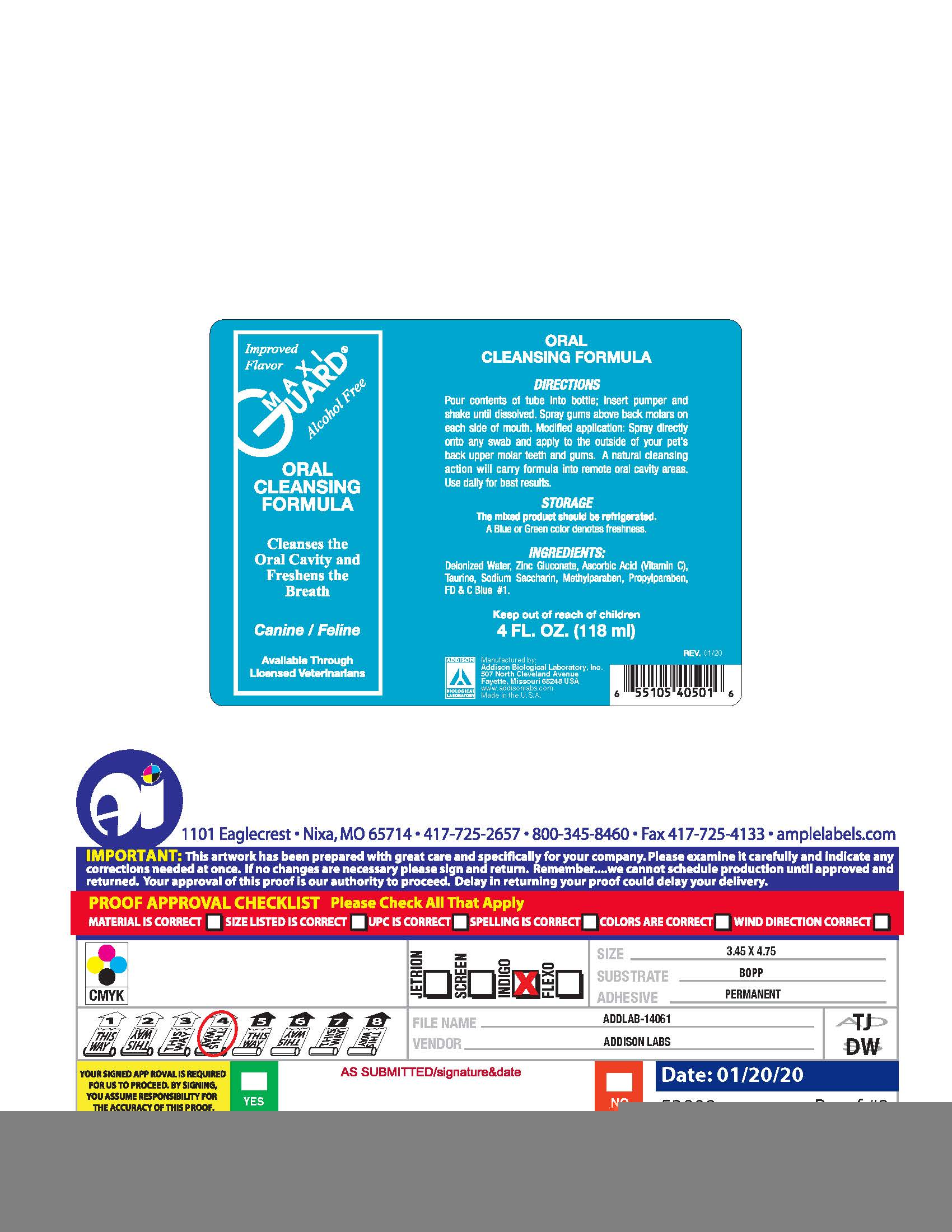 DRUG LABEL: MaxiGuard
NDC: 86045-2000 | Form: LIQUID
Manufacturer: Addison Biological Laboratory, Inc.
Category: animal | Type: OTC ANIMAL DRUG LABEL
Date: 20251201

ACTIVE INGREDIENTS: ZINC GLUCONATE 0.022 g/1 mL
INACTIVE INGREDIENTS: WATER; ASCORBIC ACID; TAURINE; SACCHARIN SODIUM; METHYLPARABEN; PROPYLPARABEN; FD&C BLUE NO. 1

MaxiGuard Oral Cleansing Formula

DIRECTIONS

Pour contents of tube into bottle; insert pumper and shake until dissolved. Spray gums above back molars on each side of the mouth. Modified application: spray directly onto any swab and apply to the outside of your pet's back upper molar teeth and gums. A natural cleansing action will carry formula into remote oral cavity areas. Use daily for best results.

STORAGE

The mixed product should be refrigerated. A Blue or Green color denotes freshness.

INACTIVE INGREDIENT

INGREDIENTS

Deionized Water, Zinc Gluconate, Ascorbic Acid (Vitamin C), Taurine, Sodium Saccharin, Methylparaben, Propylparaben, F.D.&C. Blue #1.

PACKAGE LABEL

Improved Flavor
MAXIGUARD®
Alcohol Free
ORAL
CLEANSING
FORMULA
Cleanses the
Oral Cavity and
Freshens the
Breath
Canine / Feline
Available Through Licensed Veterinarians

ORAL CLEANSING FORMULA
DIRECTIONS
Pour contents of tube into bottle; insert pumper and shake until dissolved. Spray gums above back molars on each side of the mouth. Modified application: spray directly onto any swab and apply to the outside of your pet's back upper molar teeth and gums. A natural cleansing action will carry formula into remote oral cavity areas. Use daily for best results.
STORAGE
The mixed product should be refrigerated. A Blue or Green color denotes freshness.
INGREDIENTS:
Deionized Water, Zinc Gluconate, Ascorbic Acid (Vitamin C), Taurine, Sodium Saccharin, Methylparaben, Propylparaben, F.D.&C. Blue #1.
KEEP OUT OF REACH OF CHILDREN
4 FL. OZ. (118 mL)
Manufactured by:
Addison Biological Laboratory, Inc.
507 North Cleveland Avenue
Fayette, Missouri 65248
www.addisonlabs.com
Made in the U.S.A.
REV. 01/20